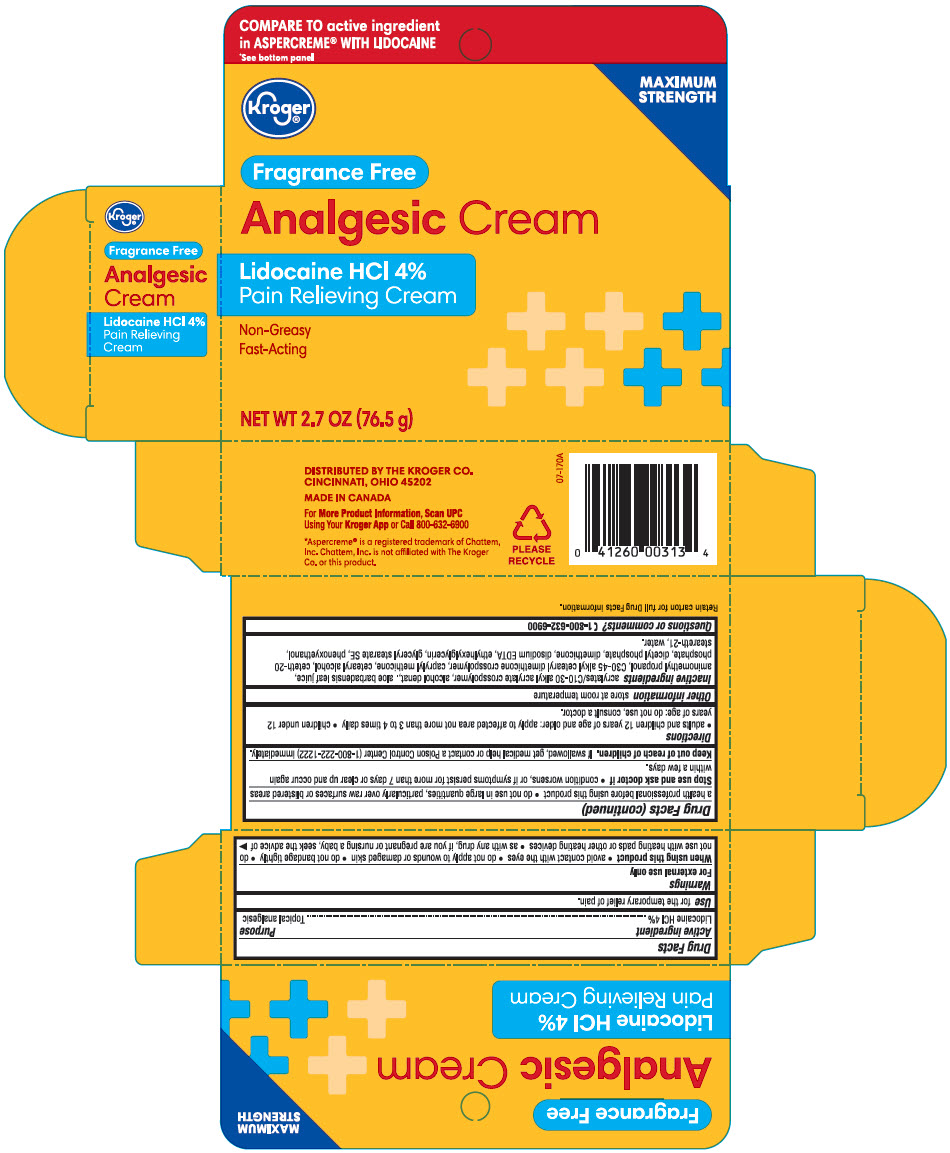 DRUG LABEL: Kroger Analgesic
NDC: 30142-260 | Form: CREAM
Manufacturer: THE KROGER CO
Category: otc | Type: HUMAN OTC DRUG LABEL
Date: 20240222

ACTIVE INGREDIENTS: Lidocaine Hydrochloride 40 mg/1 g
INACTIVE INGREDIENTS: CARBOMER INTERPOLYMER TYPE A (ALLYL SUCROSE CROSSLINKED); ALCOHOL; ALOE VERA LEAF; AMINOMETHYLPROPANOL; C30-45 Alkyl Cetearyl Dimethicone Crosspolymer; CAPRYLYL TRISILOXANE; CETOSTEARYL ALCOHOL; Ceteth-20 Phosphate; DIHEXADECYL PHOSPHATE; Dimethicone; EDETATE DISODIUM; Ethylhexylglycerin; Glyceryl Stearate SE; Phenoxyethanol; Steareth-21; Water

Kroger® Analgesic Cream
Topical Analgesic

Drug Facts

Active ingredient

Lidocaine HCl 4%

Purpose

Topical analgesic

Use

for the temporary relief of pain.

Warnings

For external use only

When using this product

- avoid contact with the eyes
- do not apply to wounds or damaged skin
- do not bandage tightly
- do not use with heating pads or other heating devices
- as with any drug, if you are pregnant or nursing a baby, seek the advice of a health professional before using this product
- do not use in large quantities, particularly over raw surfaces or blistered

Stop use and ask a doctor if

- condition worsens, or if symptoms persist for more than 7 days or clear up and occur again within a few days

Keep out of reach of children. If swallowed, get medical help or contact a Poison Control Center (1-800-222-1222) immediately.

Directions

- adults and children 12 years of age and older: apply to affected area not more than 3 to 4 times daily.
- children under 12 years of age: do not use, consult a doctor.

Other information

store at room temperature

Inactive ingredients

acrylates/C10-30 alkyl acrylate crosspolymer, alcohol denat., aloe barbadensis leaf juice, aminomethyl propanol, C30-45 alkyl cetearyl dimethicone crosspolymer, caprylyl methicone, cetearyl alcohol, ceteth-20 phosphate, dicetyl phosphate, dimethicone, disodium EDTA, ethylhexylglycerin, glyceryl stearate SE, phenoxyethanol, steareth-21, water

Questions or comments?

1-866-632-6900

DISTRIBUTED BY THE KROGER CO.
CINCINNATI, OHIO 45202

PRINCIPAL DISPLAY PANEL - 76.5 g Bottle Carton

COMPARE TO active ingredient
in ASPERCREME® WITH LIDOCAINE
*See bottom panel

MAXIMUM
STRENGTH

Kroger®

Fragrance Free

Analgesic Cream

Lidocaine HCl 4%
Pain Relieving Cream

Non-Greasy
Fast-Acting

NET WT 2.7 OZ (76.5 g)